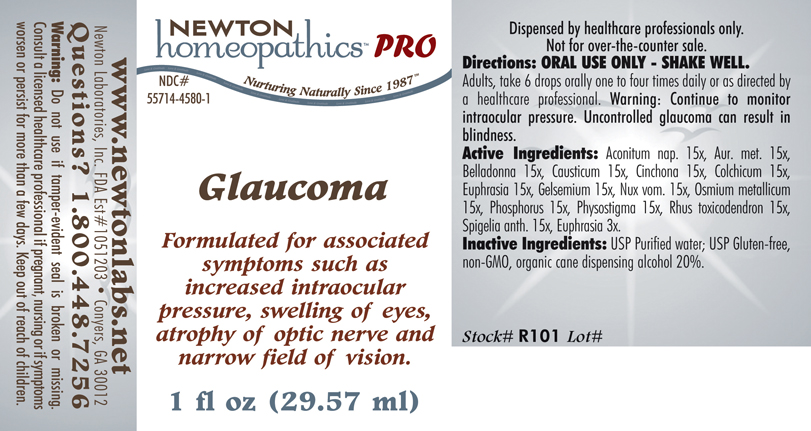 DRUG LABEL: Glaucoma 
NDC: 55714-4580 | Form: LIQUID
Manufacturer: Newton Laboratories, Inc.
Category: homeopathic | Type: HUMAN PRESCRIPTION DRUG LABEL
Date: 20110601

ACTIVE INGREDIENTS: Aconitum Napellus 15 [hp_X]/1 mL; Gold 15 [hp_X]/1 mL; Atropa Belladonna 15 [hp_X]/1 mL; Causticum 15 [hp_X]/1 mL; Cinchona Officinalis Bark 15 [hp_X]/1 mL; Colchicum Autumnale Bulb 15 [hp_X]/1 mL; Euphrasia Stricta 15 [hp_X]/1 mL; Gelsemium Sempervirens Root 15 [hp_X]/1 mL; Strychnos Nux-vomica Seed 15 [hp_X]/1 mL; Osmium 15 [hp_X]/1 mL; Phosphorus 15 [hp_X]/1 mL; Physostigma Venenosum Seed 15 [hp_X]/1 mL; Toxicodendron Pubescens Leaf 15 [hp_X]/1 mL; Spigelia Anthelmia 15 [hp_X]/1 mL
INACTIVE INGREDIENTS: Alcohol

Glaucoma

INDICATIONS & USAGE SECTION

Glaucoma Formulated for associated symptoms such as increased intraocular pressure, swelling of eyes, atrophy of optic nerve and narrow field of vision.

DOSAGE & ADMINISTRATION SECTION

Directions: ORAL USE ONLY - SHAKE WELL. Adults, take 6 drops orally one to four times daily or as directed by a healthcare professional. Warning: Continue to monitor intraocular pressure. Uncontrolled glaucoma can result in blindness.

ACTIVE INGREDIENT SECTION

Aconitum nap. 15x, Aur. met. 15x, Belladonna 15x, Causticum 15x, Cinchona 15x, Colchicum 15x, Euphrasia 15x, Gelsemium 15x, Nux vom. 15x, Osmium metallicum 15x, Phosphorus 15x, Physostigma 15x, Rhus toxicodendron 15x, Spigelia anth. 15x, Euphrasia 3x.

PURPOSE SECTION

Formulated for associated symptoms such as increased intraocular pressure, swelling of eyes, atrophy of optic nerve and narrow field of vision.

INACTIVE INGREDIENT SECTION

Inactive Ingredients: USP Purified Water; USP Gluten-free, non-GMO, organic cane dispensing alcohol 20%.

QUESTIONS? SECTION

www.newtonlabs.net Newton Laboratories, Inc. FDA Est # 1051203 - Conyers, GA 30012
Questions? 1.800.448.7256

WARNINGS SECTION

Warning: Do not use if tamper - evident seal is broken or missing. Consult a licensed healthcare professional if pregnant, nursing or if symptoms worsen or persist for more than a few days. Keep out of reach of children.

PREGNANCY OR BREAST FEEDING SECTION

Consult a licensed healthcare professional if pregnant, nursing or if symptoms worsen or persist for more than a few days.

KEEP OUT OF REACH OF CHILDREN SECTION

Keep out of reach of children.